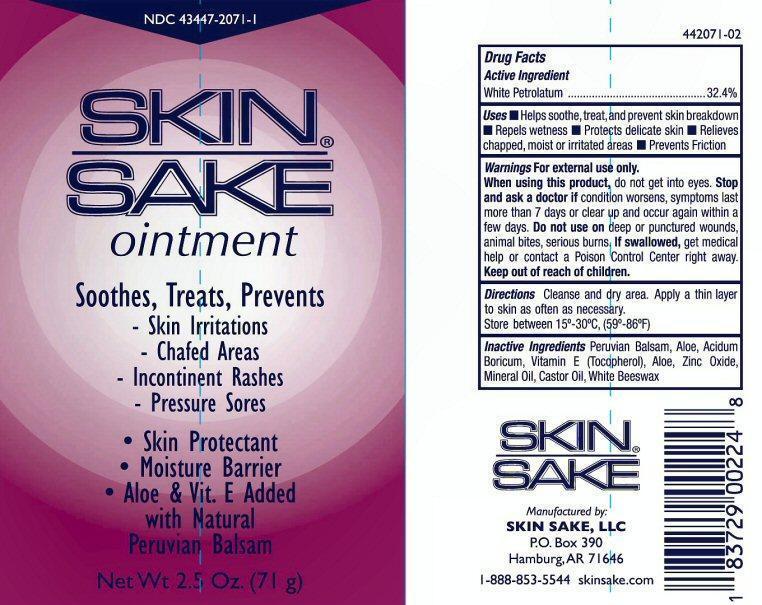 DRUG LABEL: SKIN SAKE
NDC: 43447-2071 | Form: OINTMENT
Manufacturer: Skin Sake, LLC
Category: otc | Type: HUMAN OTC DRUG LABEL
Date: 20130424

ACTIVE INGREDIENTS: PETROLATUM 23 g/71 g
INACTIVE INGREDIENTS: BALSAM PERU; ALOE; BORIC ACID; .ALPHA.-TOCOPHEROL; ZINC OXIDE; MINERAL OIL; CASTOR OIL; WHITE WAX

Active Ingredient

Drug Facts
Active Ingredient

White Petrolatum

Purpose

Soothes, Treats, Prevents,

Skin Irritations
Chafed Areas
Incontinent Rashes
Pressure Sores

Keep out of reach of children

Uses

- Helps soothe, treat , and prevent skin breakdown
- Repels wetness
- Protects delicate skin
- Relieves chapped, moist or irritated areas
- Prevents Friction

Warnings

For external use only.
When using this product, do not get into eyes.
Stop and ask a doctor if condition worsens, symptoms last more than 7 days or clear up and occur again within a few days.
Do not use on deep puncture wounds, animal bites, serious burns.
If swallowed, get medical help or contact a Poison control Center right away.

Directions

Cleanse and dry area.Apply a thin layer to skin as often as necessary.
Store between 15° - 30° C, (59° - 86° F)

Inactive ingredients

Peruvian Balsam, Aloe, Acidum Boricum, Vitamin E (Tocopherol), Zinc Oxide, Mineral Oil, Castor Oil, White Beeswax.

Product Label

NDC # 43447-2071-1
SKIN®Sake ointment
Soothes, Treats, Prevents
Skin Irritations
Chafed Areas
Incontinence Rashes
Pressure Sores

Skin Protectant
Moisture Barrier
Aloe and Vit. E Added
with Natural Peruvian Balsam

Net Wt 2.5 oz (71g)
Manufactured by:
SKIN SAKE, LLC
P.O. Box 390, Hamburg, AT 71646
1-888-853-5544 skinsake.com